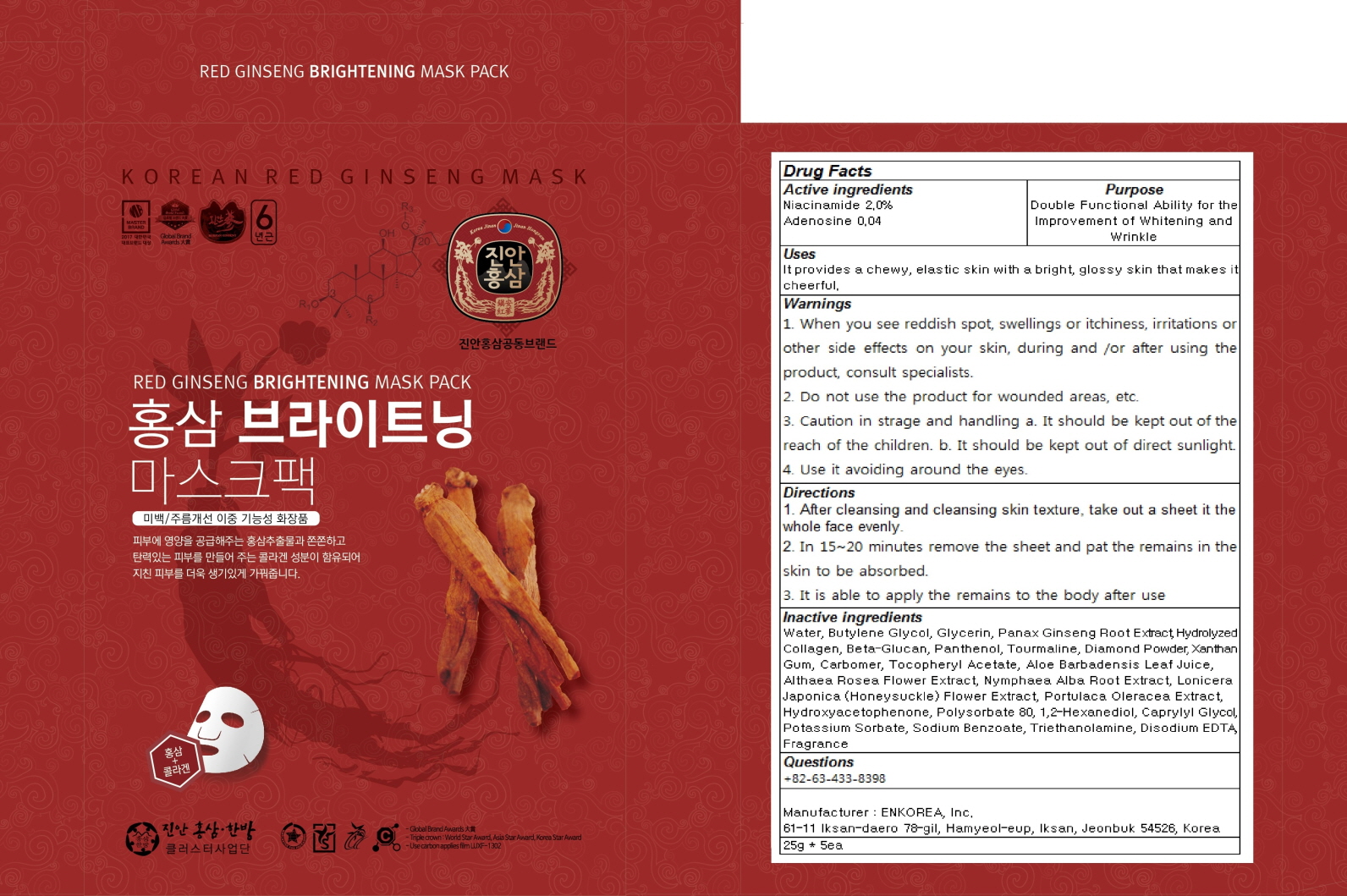 DRUG LABEL: RED GINSENG BRIGHTENING MASK PACK
NDC: 71760-020 | Form: PATCH
Manufacturer: ENKOREA, Inc.
Category: otc | Type: HUMAN OTC DRUG LABEL
Date: 20180110

ACTIVE INGREDIENTS: Niacinamide 0.50 g/25 g; Adenosine 0.01 g/25 g
INACTIVE INGREDIENTS: Water; Butylene Glycol

ACTIVE INGREDIENT

Active ingredients: Niacinamide 2.0%, Adenosine 0.04%

INACTIVE INGREDIENT

Inactive Ingredients: Water, Butylene Glycol, Glycerin, Panax Ginseng Root Extract, Hydrolyzed Collagen, Beta-Glucan, Panthenol, Tourmaline, Diamond Powder, Xanthan Gum, Carbomer, Tocopheryl Acetate, Aloe Barbadensis Leaf Juice, Althaea Rosea Flower Extract, Nymphaea Alba Root Extract, Lonicera Japonica (Honeysuckle) Flower Extract, Portulaca Oleracea Extract, Hydroxyacetophenone, Polysorbate 80, 1,2-Hexanediol, Caprylyl Glycol, Potassium Sorbate, Sodium Benzoate, Triethanolamine, Disodium EDTA, Fragrance

PURPOSE

Purpose: Double Functional Ability for the Improvement of Whitening and Wrinkle

WARNINGS

WARNINGS : 1. When you see reddish spot, swellings or itchiness, irritations or other side effects on your skin, during and /or after using the product, consult specialists. 2. Do not use the product for wounded areas, etc. 3. Caution in strage and handling a. It should be kept out of the reach of the children. b. It should be kept out of direct sunlight. 4. Use it avoiding around the eyes.

KEEP OUT OF REACH OF CHILDREN

It should be kept out of the reach of the children.

USES

USES: It provides a chewy, elastic skin with a bright, glossy skin that makes it cheerful.

DIRECTIONS

DIRECTIONS: 1. After cleansing and cleansing skin texture, take out a sheet it the whole face evenly. 2. In 15~20 minutes remove the sheet and pat the remains in the skin to be absorbed. 3. It is able to apply the remains to the body after use.

QUESTIONS

Questions: +82-63-433-8398